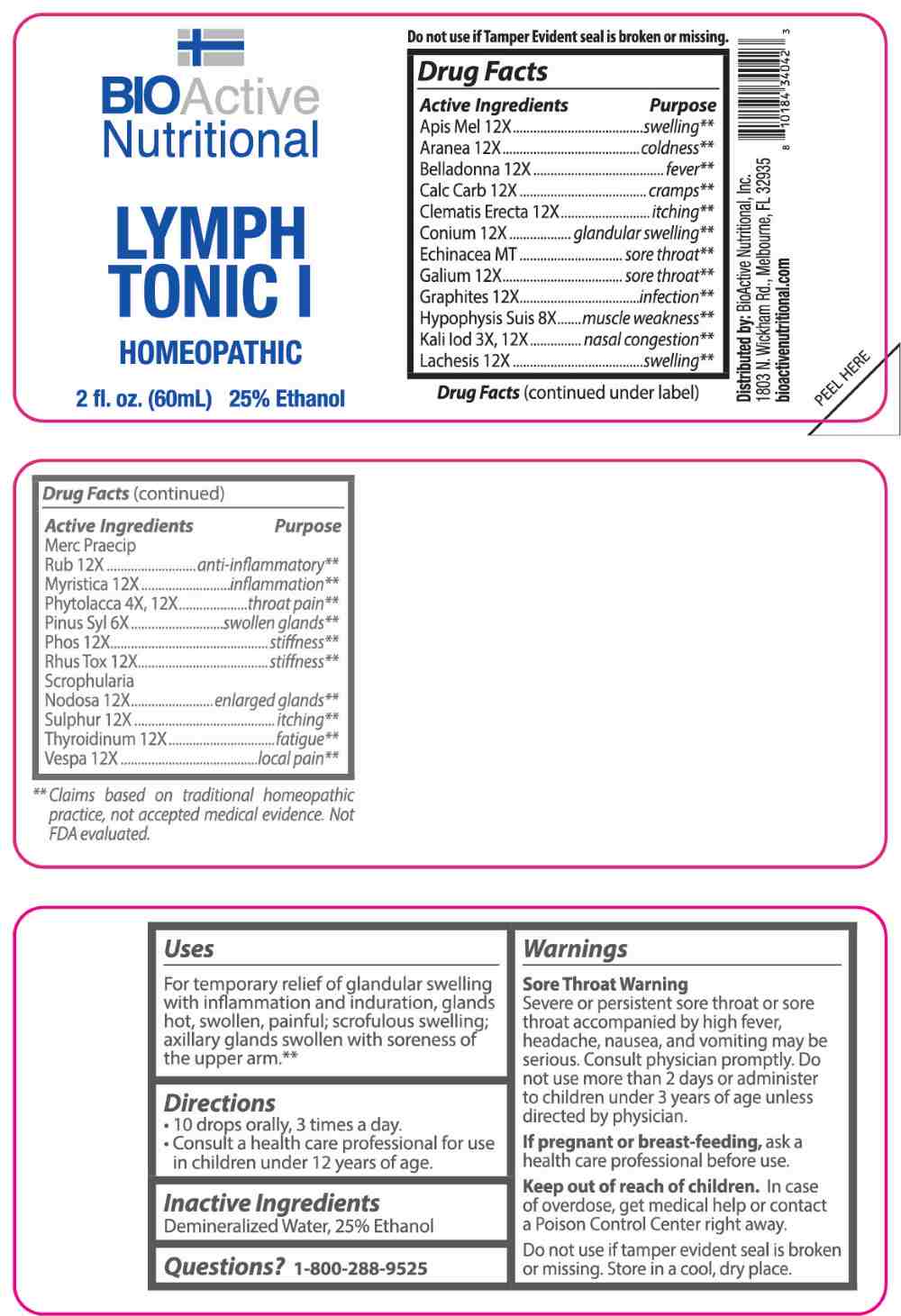 DRUG LABEL: Lymph Tonic
NDC: 43857-0657 | Form: LIQUID
Manufacturer: BioActive Nutritional, Inc.
Category: homeopathic | Type: HUMAN OTC DRUG LABEL
Date: 20250603

ACTIVE INGREDIENTS: ECHINACEA ANGUSTIFOLIA WHOLE 1 [hp_X]/1 mL; POTASSIUM IODIDE 3 [hp_X]/1 mL; PHYTOLACCA AMERICANA ROOT 4 [hp_X]/1 mL; PINUS SYLVESTRIS LEAFY TWIG 6 [hp_X]/1 mL; SUS SCROFA PITUITARY GLAND 8 [hp_X]/1 mL; APIS MELLIFERA 12 [hp_X]/1 mL; ARANEUS DIADEMATUS 12 [hp_X]/1 mL; ATROPA BELLADONNA 12 [hp_X]/1 mL; OYSTER SHELL CALCIUM CARBONATE, CRUDE 12 [hp_X]/1 mL; CLEMATIS RECTA FLOWERING TOP 12 [hp_X]/1 mL; CONIUM MACULATUM FLOWERING TOP 12 [hp_X]/1 mL; GALIUM APARINE WHOLE 12 [hp_X]/1 mL; GRAPHITE 12 [hp_X]/1 mL; LACHESIS MUTA VENOM 12 [hp_X]/1 mL; MERCURIC OXIDE 12 [hp_X]/1 mL; VIROLA SEBIFERA RESIN 12 [hp_X]/1 mL; PHOSPHORUS 12 [hp_X]/1 mL; TOXICODENDRON PUBESCENS LEAF 12 [hp_X]/1 mL; SCROPHULARIA NODOSA WHOLE 12 [hp_X]/1 mL; SULFUR 12 [hp_X]/1 mL; THYROID 12 [hp_X]/1 mL; VESPA CRABRO 12 [hp_X]/1 mL
INACTIVE INGREDIENTS: WATER; ALCOHOL

DRUG FACTS:

ACTIVE INGREDIENTS:

Apis Mellifica 12X, Aranea Diadema 12X, Belladonna 12X, Calcarea Carbonica 12X, Clematis Erecta 12X, Conium Maculatum 12X, Echinacea MT, Galium Aparine 12X, Graphites 12X, Hypophysis Suis 8X, Kali Iodatum 3X, 12X, Lachesis Mutus 12X, Mercurius Praecipitatus Ruber 12X, Myristica Sebifera 12X, Phytolacca Decandra 4X, 12X, Pinus Sylvestris 6X, Phosphorus 12X, Rhus Tox 12X, Scrophularia Nodosa 12X, Sulphur 12X, Thyroidinum 12X, Vespa Crabro 12X.

PURPOSE:

Apis Mellifica - swelling,** Aranea Diadema - coldness,** Belladonna - fever,** Calcarea Carbonica - cramps,** Clematis Erecta - itching,** Conium Maculatum – glandular swelling,** Echinacea – sore throat,** Galium Aparine – sore throat,** Graphites - infection,** Hypophysis Suis – muscle weakness,** Kali Iodatum – nasal congestion,** Lachesis Mutus - swelling,** Mercurius Praecipitatus Ruber – anti-inflammatory,** Myristica Sebifera - inflammation,** Phytolacca Decandra – throat pain,** Pinus Sylvestris – swollen glands,** Phosphorus - stiffness,** Rhus Tox - stiffness,** Scrophularia Nodosa – enlarged glands,** Sulphur - itching,** Thyroidinum - fatigue,** Vespa Crabro – local pain**

**Claims based on traditional homeopathic practice, not accepted medical evidence. Not FDA evaluated.

USES:

For temporary relief of glandular swelling with inflammation and induration, glands hot, swollen, painful; scrofulous swelling; axillary glands swollen with soreness of the upper arm.**

**Claims based on traditional homeopathic practice, not accepted medical evidence. Not FDA evaluated.

WARNINGS:

Sore Throat Warning

Severe or persistent sore throat or sore throat accompanied by high fever, headache, nausea, and vomiting may be serious. Consult physician promptly. Do not use more than 2 days or administer to children under 3 years of age unless directed by physician.
If pregnant or breast-feeding, ask a health care professional before use.

Keep out of reach of children. In case of overdose, get medical help or contact a Poison Control Center right away.

Do not use if tamper evident seal is broken or missing.

Store in a cool, dry place.

KEEP OUT OF REACH OF CHILDREN:

In case of overdose, get medical help or contact a Poison Control Center right away.

DIRECTIONS:

• 10 drops orally, 3 times a day.

• Consult a health care professional for use in children under 12 years of age.

INACTIVE INGREDIENTS:

Demineralized Water, 25% Ethanol

QUESTIONS:

Distributed by:
BioActive Nutritional, Inc.
1803 N. Wickham Rd.
Melbourne, FL 32935
bioactivenutritional.com

1-800-288-9525

PACKAGE LABEL DISPLAY:

BIOActive Nutritional

LYMPH TONIC I

HOMEOPATHIC

2 fl. oz. (60mL)